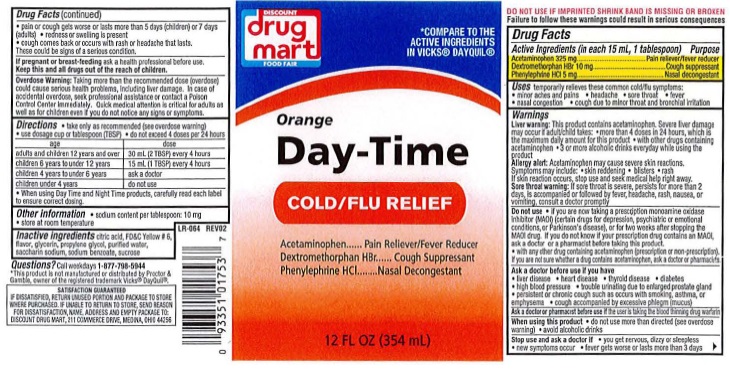 DRUG LABEL: Day-Time COLD/FLU RELIEF
NDC: 53943-506 | Form: LIQUID
Manufacturer: Discount Drug Mart
Category: otc | Type: HUMAN OTC DRUG LABEL
Date: 20251219

ACTIVE INGREDIENTS: ACETAMINOPHEN 325 mg/15 mL; DEXTROMETHORPHAN HYDROBROMIDE 10 mg/15 mL; PHENYLEPHRINE HYDROCHLORIDE 5 mg/15 mL
INACTIVE INGREDIENTS: ANHYDROUS CITRIC ACID; FD&C YELLOW NO. 6; GLYCERIN; PROPYLENE GLYCOL; WATER; SACCHARIN SODIUM; SODIUM BENZOATE; SUCROSE

Orange Day-Time COLD/FLU RELIEF

Drug Facts Active Ingredients (in each 15 mL, 1 tablespoon)

Acetaminophen 325 mg

Dextromethorphan HBr 10 mg

Phenylephrine HCL 5 mg

Purpose

Pain reliever/fever reducer

Cough suppressant

Nasal decongestant

Keep out of reach of children

Keep this and all drugs out of the reach of children.

Uses

temporaily relieves these common cold/flu symptoms:

- minor aches and pains
- headache
- sore throat
- fever
- nasal congestion
- cough due to minor throat and bronchial irritation

Warnings

Liver warning:This product contains acetaminophen. Severe liver damage
may occur if adult/child takes: ● more than 4 doses in 24 hours, which is
the maximum daily amount for this product ● with other drugs containing
acetaminophen ● 3 or more alcoholic drinks everyday while using this product.
Allery Alert:Acetaminophen may cause severe skin reactions.
Symptoms may include: ● skin reddening ● blisters ● rash
If skin reaction occurs, stop use and seek medical help right away.
Sore throat warning:If sore throat is severe, persists for more than
2 days, is accompanied or followed by fever, headache, rash,
Nausea, or vomiting, consult a doctor promptly.

Do not use

- if you are now taking a prescription monamine oxidase inhibitor (MAOI) (certain drugs for depression psychiatric or emotional conditions, or Parkinson's disease), or for 2 weeks after stopping the MAOI drug. If you do not know if your prescription drug contains an MAOI, ask a doctor or pharmacist before taking this product.
- with any other drug containing acetaminophen (prescription or nonprescription) If you are not sure whether a drug contains acetaminophen, ask a doctor or pharmacist

Ask a doctor before use if you have

- liver disease
- heart disease
- thyroid disease
- diabetes
- high blood pressure
- trouble urinating due to enlarged prostate gland
- persistant or chronic cough such as occur with smoking, asthma, or emphysema
- cough accompanied by excessive phlegm (mucuc)

Ask a doctor or pharmacist before use if

the user is taking the blood thinner warfarin

When using this product

- do not use more than directed (see overdose warning)
- avoid alcoholic drinks

Stop use and ask a doctor if

- you get nervous, dizzy or sleepless
- new symptoms occur
- fever gets worse or lasts more than 3 days
- pain or cough gets worse or lasts more than 5 days (children) 7 days (adults)
- redness or swelling is present
- cough comes back or occurs with rash or headache that lasts.

These could be signs of a serious condition.

If pregnant or breast-feeding

ask a health professional before use.

Overdose warning:

Taking more than the recommended dose (overdose) could cause serious health problems, including liver damage. In case of accidental overdose, seek professional assistance or contact a Poison Control Center immediately. Quick medical attention is critical for adults as well as for children even if you do not notice any signs or symptoms.

Directions

- take only as recommended (see overdose warning)
- use dosage cup or tablespoon (TBSP)
- do not exceed 4 doses per 24 hours

age | dose
adults and children 12 years and over | 30 mL (2 TBSP) every 4 hours
children 6 years to under 12 years | 15 mL (1 TBSP) every 4 hours
children 4 years to under 6 years | ask a doctor
children under 4 years | do not use

* When using Day Time and Night Time products, carefully read each label to ensure correct dosing.

Other information

- sodium content per tablespoon: 10 mg
- store at room temperature

DO NOT USE IF IMPRINTED SHRINK BRAND IS MISSING OR BROKEN
Failure to follow these warnings could result in serious consequences.

Inactive ingredients

citric acid, FD and C Yellow # 6, flavor, glycerin, propylene glycol, prified water, saccharin sodium, sodium benzoate, sucrose

Questions?

Call weekdays 1-877-798-5944

Product Label: DISCOUNT drug mart FOOD FAIR Orange Day-Time COLD/FLU RELIEF

*COMPARE TO THE ACTIVE INGREDIENTS IN VICKS®DAYQUIL®

DISCOUNT

drug mart

FOOD FAIR

Orange Day-Time Cold/Flu Relief

Acetaminophen ...... Pain Reliever/Fever Reducer

Dextromethorphan HBR ....... Cough Suppressant

Phenylephrine HCL ....... Nasal Decongestant

12 FL OZ (354 mL)

* This product is not manufactured or distributed by Proctor and Gamble owner of the registered trademark Vicks®DayQuil®

LR-064 REV 02

SATISFACTION GUARANTEED

IF DISSATISFIED, RETURN UNUSED PORTION AND PACKAGE TO THE STORE WHERE PURCHASED. IF UNABLE TO RETURN TO THE STORE, SEND REASON FOR DISSATISFACTION , NAME, ADDRESS AND EMPTY PACKAGE TO: DISCOUNT DRUG MART, 211 COMMERCE DRIVE MEDINNA, OHIO 44256

res